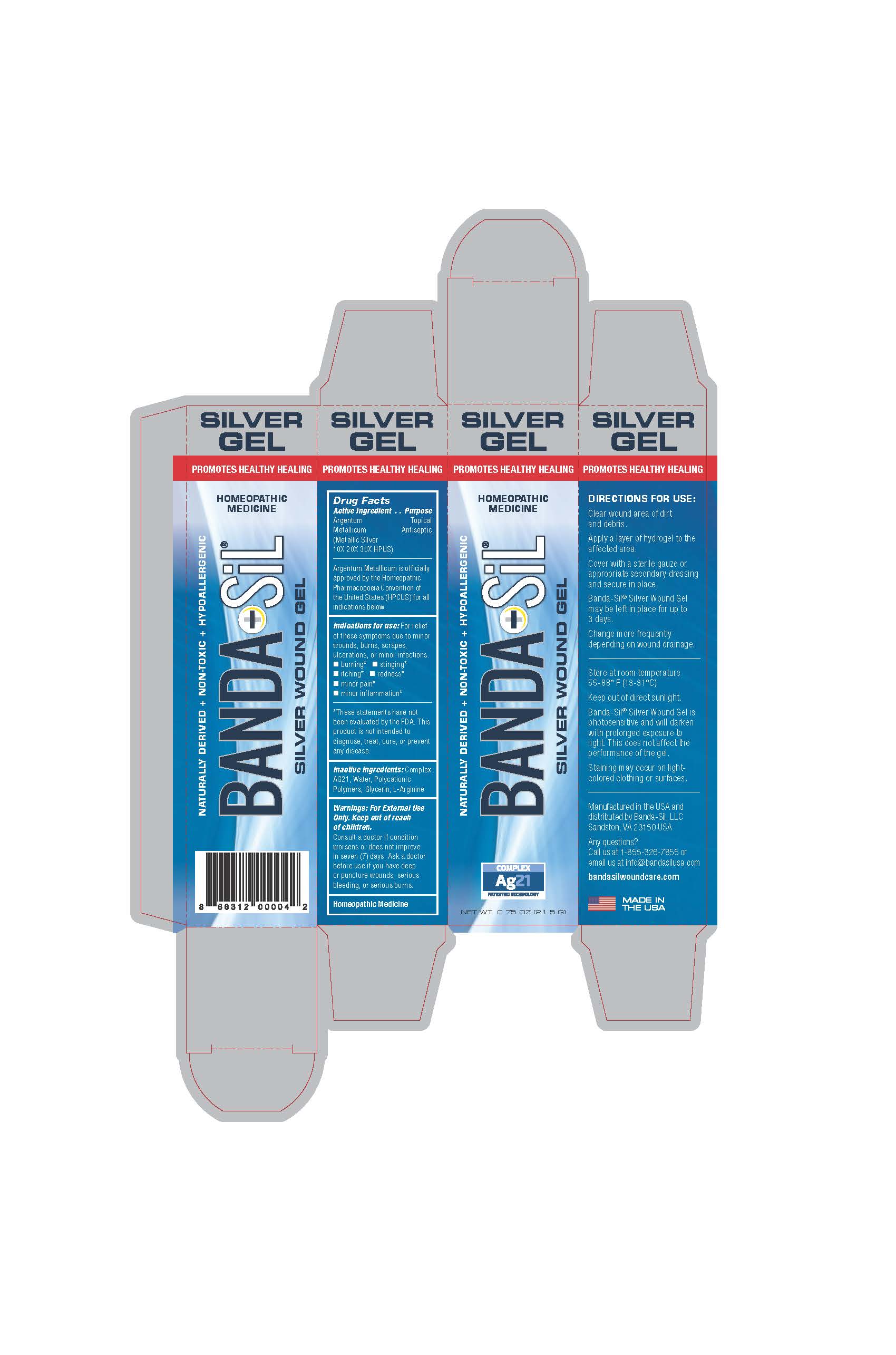 DRUG LABEL: Banda-Sil Gel Silver Wound Dressing
NDC: 72363-004 | Form: GEL
Manufacturer: AG Essence Inc
Category: homeopathic | Type: HUMAN OTC DRUG LABEL
Date: 20240419

ACTIVE INGREDIENTS: SILVER 1 g/21.5 g
INACTIVE INGREDIENTS: ARGININE 0.215 g/21.5 g; WATER 16.835 g/21.5 g; POLYQUATERNIUM-4 (1600 MPA.S AT 2%) 1.5 g/21.5 g; GLYCERIN 1.95 g/21.5 g

Directions:
Clean wound area of dirt and debris. Apply a layer of hydrogel to the affected area. Cover with a sterile gauze or appropriate secondary dressing and secure in place. Banda-Sil Silver Wound Gel may be left in place for up to 3 days. Change more frequently depending on wound drainage.
Indications for use:
For relief of symptoms due to wounds, burns, scrapes, ulcerations or minor infections.
Disclaimer: These statements have not been evaluated by the FDA. This product is not intended to diagnose, treat, cure or prevent any disease.

WARNINGS

Warnings: For external use only. Keep out of reach of children. Consult a doctor if condition worsens or does not improve in seven (7) days. Ask a doctor for before use if you have deep or puncture wounds serious blleding or serious burns.

INACTIVE INGREDIENT

Complex Ag 21, Agua, Polycationic Polymers, Glycerin, L-Arginine

INDICATIONS AND USAGE

Indications: For relief of these symptoms due to minor wounds, burns, scrapes, ulcerations or minor infections.

Burning Stinging

Itching Redness

Minor Pain

Minor Inflamation

KEEP OUT OF REACH OF CHILDREN

Warnings: For external use only. Keep out of reach of children.

PURPOSE

Topical Antiseptic

Homeopathic Medicine

ACTIVE INGREDIENT

Active: Argentum Metallcum (Metallic Silver 10X 20X 30X HPUS)

Banda-Sil Silver Wound Gel Box

Homeopathic Drug

Banda-Sil Silver Wound Gel
Ingredients:
ACTIVE: Argentum Metallicum 10x, 20x and 30x HPUS
INACTIVE: Ag21 Complex, Aqua, Polycationic Polymers, Glycerin, L-Arginine

Purpose
Gel Wound Dressing
Homeopathic medicine
Warnings:
For external use only
Keep out of reach of children